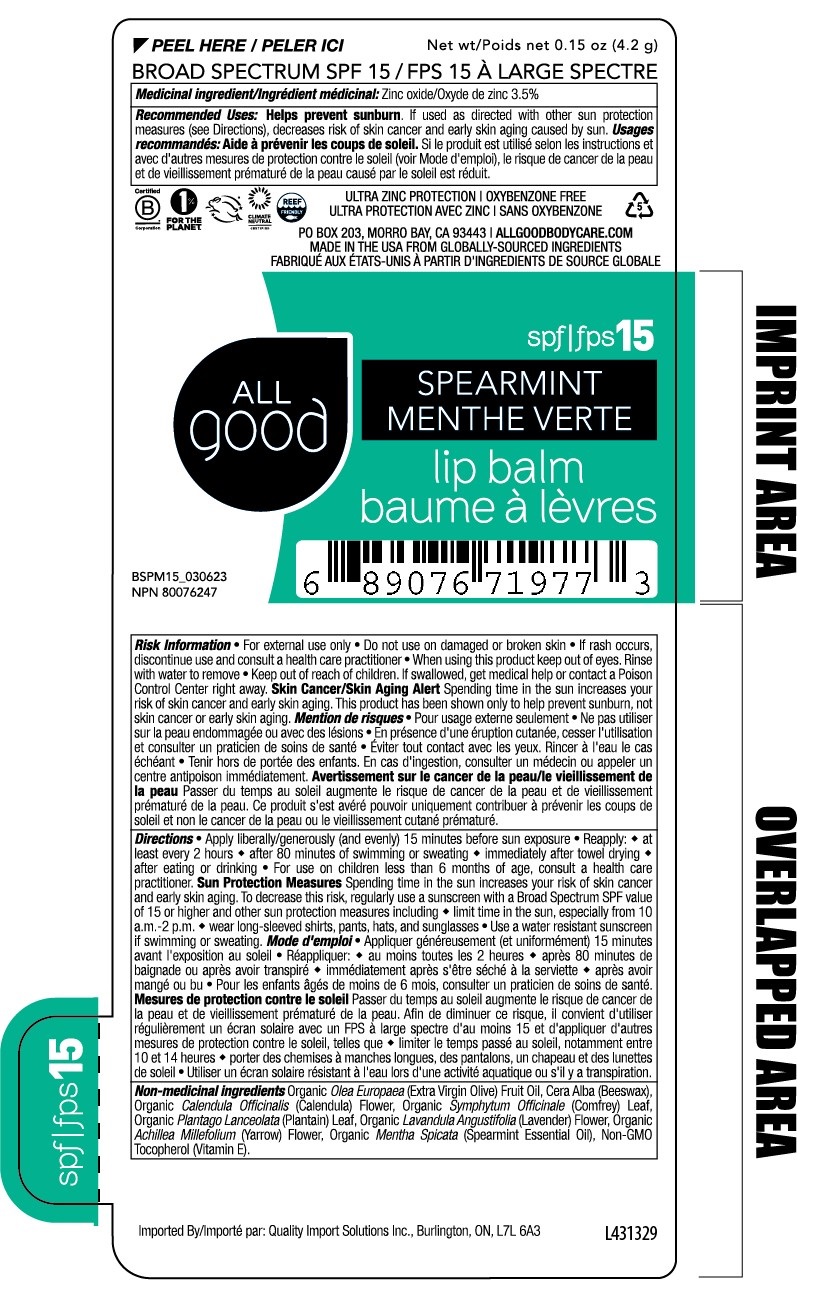 DRUG LABEL: All Good Broad Spectrum SPF 15 Spearmint Lip Balm
NDC: 65692-0313 | Form: STICK
Manufacturer: Raining Rose, Inc.
Category: otc | Type: HUMAN OTC DRUG LABEL
Date: 20231103

ACTIVE INGREDIENTS: ZINC OXIDE 35 mg/1 g
INACTIVE INGREDIENTS: CALENDULA OFFICINALIS FLOWER; COMFREY LEAF; LAVANDULA ANGUSTIFOLIA FLOWER; PLANTAGO MAJOR LEAF; ACHILLEA MILLEFOLIUM FLOWER; OLIVE OIL; YELLOW WAX; SPEARMINT OIL; TOCOPHEROL

All Good Broad Spectrum SPF 15 Spearmint Lip Balm

ACTIVE INGREDIENT

Medicinal ingredients: Zinc Oxide 3.5%

Purpose

Sunscreen

INDICATIONS AND USAGE

Recommended Uses: Helps prevent sunburn.If used as directed with other sun protection measures (see Directions), decreases risk of skin cancer and early skin aging caused by sun.

WARNINGS

Risk Information • For external use only • Do not use on damaged or broken skin • If rash occurs, discontinue use and consult a health care practitioner • When using this product keep out of eyes. • Rinse with water to remove.

Skin Cancer/Skin Aging Alert Spending time in the sun increases your risk of skin cancer and early skin aging. This product has been shown only to help prevent sunburn, skin cancer or early skin aging.

Keep out of reach of children. If swallowed, get medical help or call a Poison Control Center right away.

DOSAGE AND ADMINISTRATION

Directions • Apply liberally/generously (and evenly) 15 minutes before sun exposure. • Reapply: • at least every 2 hours • after 80 minutes of swimming or sweating • immediately after towel drying • after eating or drinking • For use on children less than 6 months of age, consult a health care practitioner. Sun Protection Measures Spending time in the sun increases your risk of skin cancer and early skin aging. To decrease this risk, regularly use a sunscreen with a Broad Spectrum SPF value of 15 or higher and other sun protection measures including • limit time in the sun, especially from 10 a.m.,-2 p.m. • wear long-sleeved shirts, pants, hats, and sunglasses • Use a water resistant sunscreen if swimming or sweating.

INACTIVE INGREDIENT

Non-medicinal Ingredients: Organic Olea Europaea (Extra Virgin Olive) Fruit Oil, Cera Alba (Beeswax), Organic Calendula Officinalis (Calendula) Flower, Organic Symphytum Officinale (Comfrey) Leaf, Organic Plantago Lanceolata (Plantain) Leaf, Organic Lavandula Angustifolia (Lavender) Flower, Organic Achillea Millefolium (Yarrow) Flower, Organic Mentha Spicata (Spearmint Essential Oil), Non-GMO Tocopherol (Vitamin E).

Product Package Labeling

BROAD SPECTRUM SPF 15

ALL

good

SPEARMINT

lip balm

Net wt 0.15 oz (4.2 g)

P.O. BOX 203, MORRO BAY, CA 93443 | ALLGOODBODYCARE.COM

res